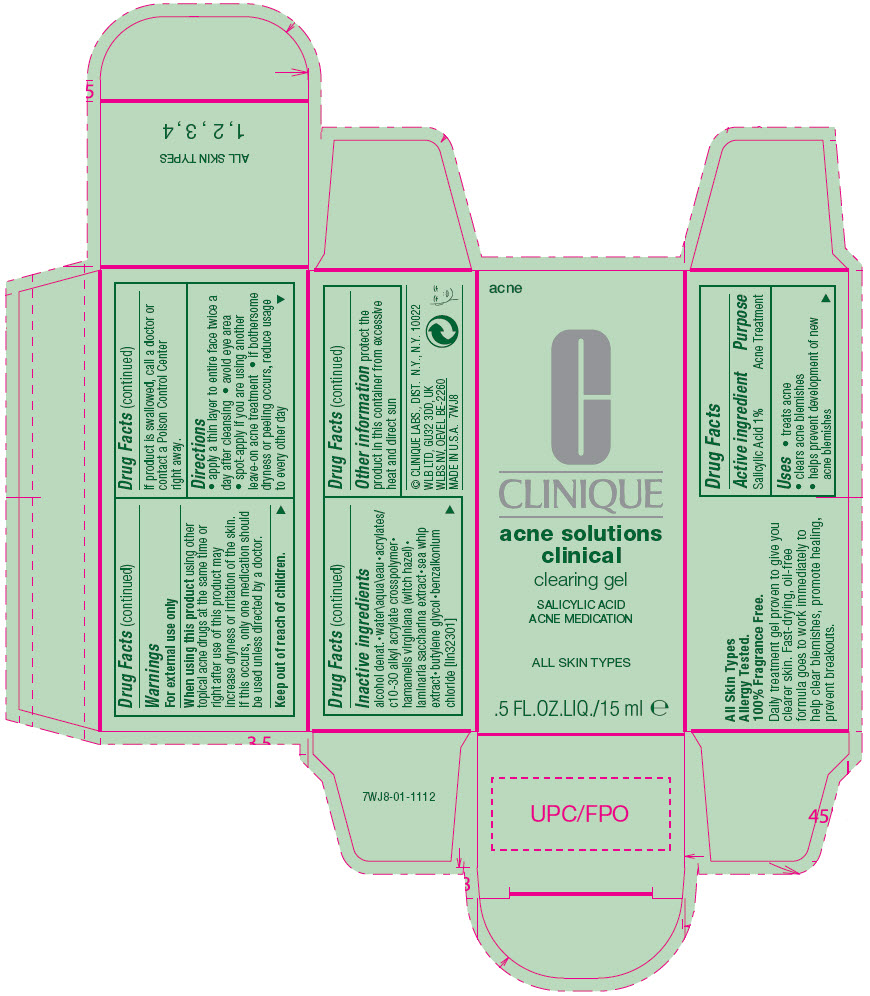 DRUG LABEL: ACNE SOLUTIONS
NDC: 49527-825 | Form: GEL
Manufacturer: CLINIQUE LABORATORIES LLC
Category: otc | Type: HUMAN OTC DRUG LABEL
Date: 20260226

ACTIVE INGREDIENTS: SALICYLIC ACID 10 mg/1 mL
INACTIVE INGREDIENTS: ALCOHOL; WATER; CARBOMER INTERPOLYMER TYPE A (ALLYL SUCROSE CROSSLINKED); WITCH HAZEL; SACCHARINA LATISSIMA; PSEUDOPTEROGORGIA ELISABETHAE; BUTYLENE GLYCOL; BENZALKONIUM CHLORIDE

ACNE SOLUTIONS
SPOT HEALING ACNE MEDICATION

Drug Facts

Active ingredient

Salicylic Acid 1%

Purpose

Acne Treatment

Uses

- treats acne
- clears acne blemishes
- helps prevent development of new acne blemishes

Warnings

For external use only

When using this product using other topical acne drugs at the same time or right after use of this product may increase dryness or irritation of the skin. If this occurs, only one medication should be used unless directed by a doctor.

Keep out of reach of children.

If product is swallowed, call a doctor or contact a Poison Control Center right away.

Directions

- apply a thin layer to entire face twice a day after cleansing
- avoid eye area
- spot-apply if you are using another leave-on acne treatment
- if bothersome dryness or peeling occurs, reduce usage to every other day

Inactive ingredients

alcohol denat.•water\aqua\eau•acrylates/c10-30 alkyl acrylate crosspolymer•hamamelis virginiana (witch hazel)•laminaria saccharina extract•sea whip extract•butylene glycol•benzalkonium chloride [iln32301]

Other information

protect the product in this container from excessive heat and direct sun

PRINCIPAL DISPLAY PANEL - 15 ml Tube Carton

acne

CLINIQUE

acne solutions
clinical

clearing gel

SALICYLIC ACID
ACNE MEDICATION

ALL SKIN TYPES

.5 FL.OZ.LIQ./15 ml e